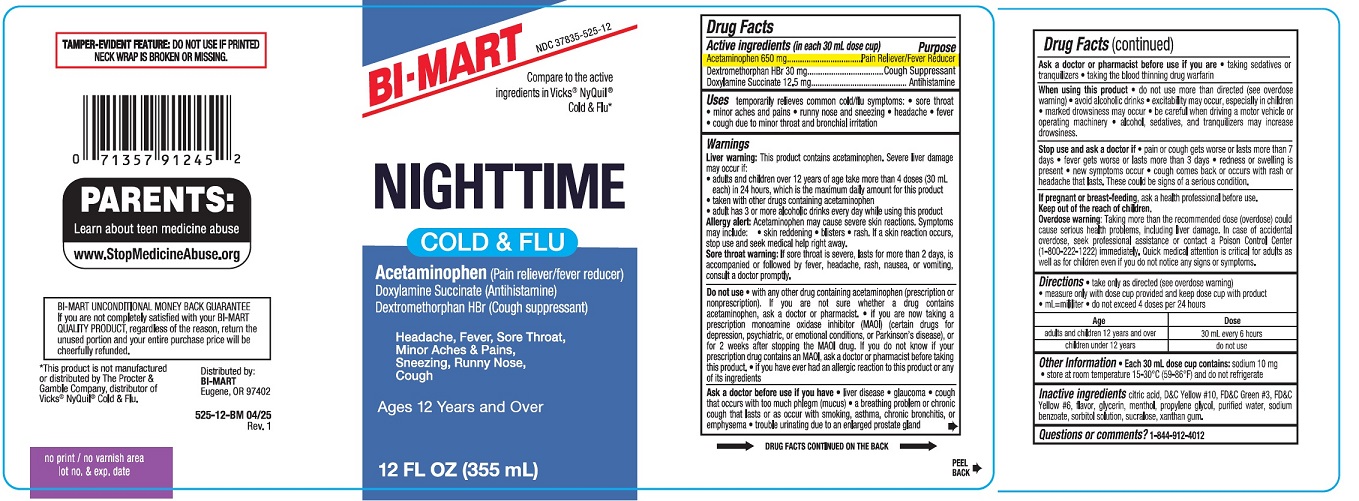 DRUG LABEL: NIGHTTIME COLD AND FLU
NDC: 37835-525 | Form: LIQUID
Manufacturer: BI-MART
Category: otc | Type: HUMAN OTC DRUG LABEL
Date: 20250501

ACTIVE INGREDIENTS: ACETAMINOPHEN 650 mg/30 mL; DEXTROMETHORPHAN HYDROBROMIDE 30 mg/30 mL; DOXYLAMINE SUCCINATE 12.5 mg/30 mL
INACTIVE INGREDIENTS: PROPYLENE GLYCOL; SODIUM BENZOATE; XANTHAN GUM; GLYCERIN; D&C YELLOW NO. 10; WATER; FD&C GREEN NO. 3; SUCRALOSE; MENTHOL; ANHYDROUS CITRIC ACID; SORBITOL SOLUTION 70%; FD&C YELLOW NO. 6

NIGHTTIME COLD & FLU

Drug Facts

Active ingredients (in each 30 mL dose cup)

Acetaminophen 650 mg

Dextromethorphan HBr 30 mg

Doxylamine Succinate 12.5 mg

Purpose

Pain Reliever/Fever Reducer

Cough Suppressant

Antihistamine

Uses

temporarily relieves common cold/flu symptoms:

• sore throat

• minor aches and pains

• runny nose and sneezing

• headache

• fever

• cough due to minor throat and bronchial irritation.

Warnings

Liver warning:This product contains acetaminophen. Severe liver damage may occur if:

• adults and children over 12 years of age take more than 4 doses (30 mL each) in 24 hours, which is the maximum daily amount for this product
• taken with other drugs containing acetaminophen
• adult has 3 or more alcoholic drinks every day while using this product.

Allergy alert:Acetaminophen may cause severe skin reactions. Symptoms may include:

• skin reddening

• blisters

• rash. If a skin reaction occurs, stop use and seek medical help right away.

Sore throat warning:If sore throat is severe, lasts for mroe than 2 days, is accompanied or followed by fever, heacache, rash, nausea, or vomiting, consult a doctor promptly.

Do not use

• with any other drug containing acetaminophen (prescription or nonprescription). If you are not sure whether a drug contains acetaminophen, ask a doctor or pharmacist.

• if you are now taking a prescription monoamine oxidase inhibitor (MAOI) (certain drugs for depression, psychiatric, or emotional conditions, or Parkinson’s disease), or for 2 weeks after stopping the MAOI drug. If you do not know if your prescription drug contains an MAOI, ask a doctor or pharmacist before taking this product.

• if you have ever had an allergic reaction to this product or anay of its ingredients

Ask a doctor before use if you have

• liver disease

• glaucoma

• cough that occurs with too much phlegm (mucus)

• a breathing problem or chronic cough that lasts or as occur with smoking, asthma, chronic bronchitis or emphysema

• trouble urinating due to an enlarged prostate gland.

Ask a doctor or pharmacist before use if you are

- taking sedatives or tranquilizers
- taking the blood thinning drug warfarin.

When using this product

• do not use more than directed (see overdose warning)

• avoid alcoholic drinks

• excitability may occur, especially in children

• marked drowsiness may occur

• be careful when driving a motor vehicle or operating machinery

• alcohol, sedatives, and tranquilizers may increase drowsiness.

Stop use and ask a doctor if

• pain or cough gets worse or lasts more than 7 days

• fever gets worse or lasts more than 3 days

• redness or swelling is present

• new symptoms occur

• cough comes back or occurs with rash or headache that lasts. These could be signs of a serious condition.

If pregnant or breast-feeding,

ask a health professional before use.

Keep out of the reach of children.

Overdose warning:

Taking mroe than the recommended dose (overdose) could cause serious health problems, including liver damage. In case of accidental overdose, seek professional assistance or contact a Poison Control Center (1-800-222-1222) immediately.Quick medical attention is critical for adults as well as for children even if you do not notice any signs or symptoms.

Directions

• take only as directed (see overdose warning)

• measure only with dosing cup provided and keep dosage cup with product

• mL=mililiter

• do not exceed 4 doses per 24 hours

Age | Dose
adults and children 12 years and over | 30 mL every 6 hours
children under 12 years | do not use

Other Information

• Each 30 mL dose cup contains:sodium 10 mg

• store at room temperature 15-30°C (59-86°F) and do not refrigerate

Inactive ingredients

citric acid, D&C Yellow #10, FD&C Green #3, FD&C Yellow #6, flavor, glycerin, menthol, propylene glycol, purified water, sodium benzoate, sorbitol solution, sucralose, xanthan gum.

Questions or comments?

1-844-912-4012